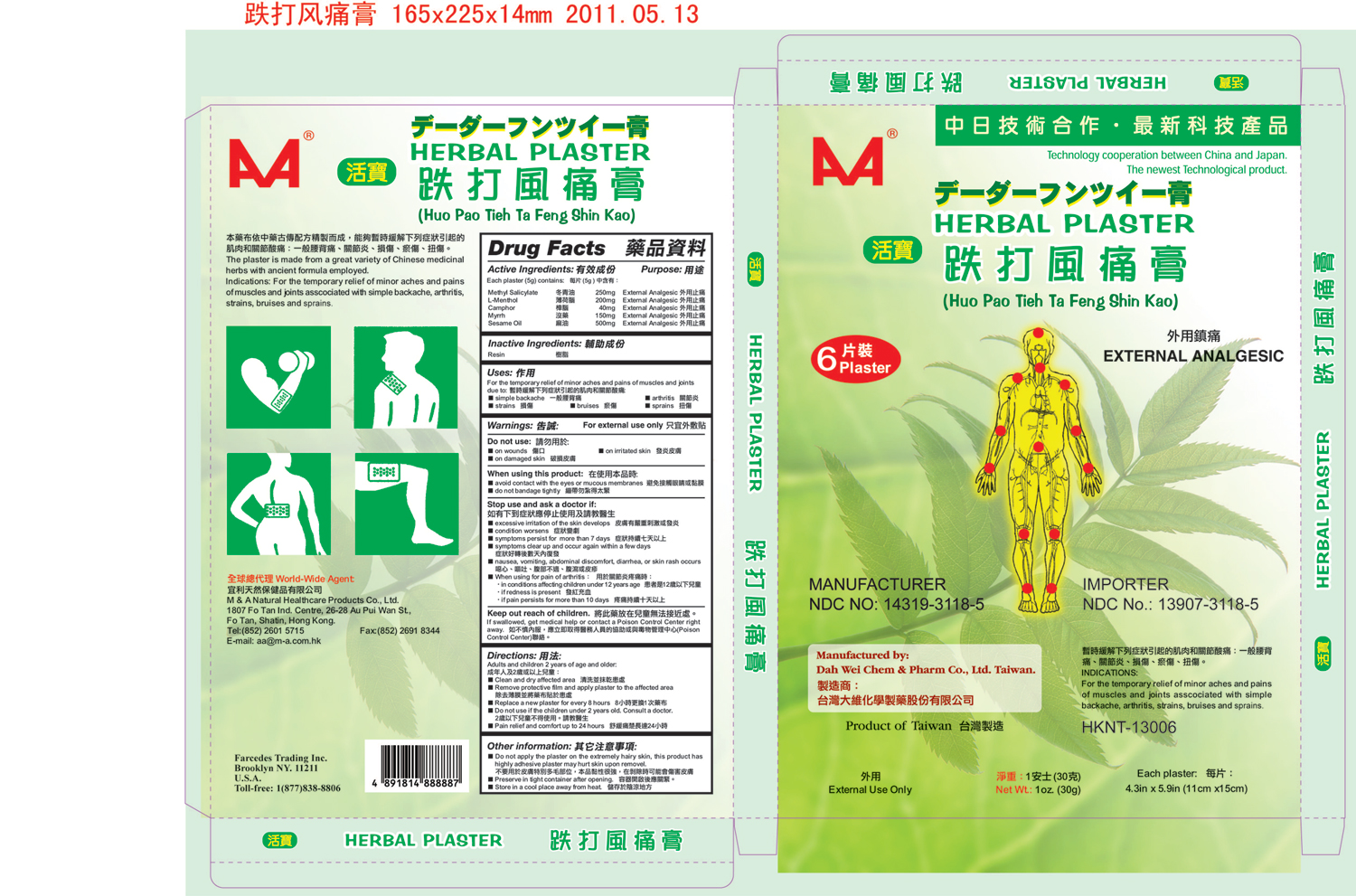 DRUG LABEL: Plaster
NDC: 14319-3118 | Form: PATCH
Manufacturer: Dah Wei Chem & Pharm Co., Ltd.
Category: otc | Type: HUMAN OTC DRUG LABEL
Date: 20110608

ACTIVE INGREDIENTS: MENTHOL 1.2 g/30 g; METHYL SALICYLATE 1.5 g/30 g; CAMPHOR (SYNTHETIC) 0.24 g/30 g; MYRRH .90 g/30 g; SESAME OIL 3.00 g/30 g
INACTIVE INGREDIENTS: PINUS TABULIFORMIS BARK

MandAHerbalPlaster

Active ingredients: (each 5 g patch contains) PURPOSE
METHYL SALICYLATE 250 mg EXTERNAL ANALGESIC
L-METHENOL - 200 mg EXTERNAL ANALGESIC
CAMPHOR – 40mg EXTERNAL ANALGESIC
SESAME OIL – 500 mg EXTERNAL ANALGESIC
MYRRH – 150mg EXTERNAL ANALGESIC

INDICATIONS AND USAGE

for the temporary relief of minor aches and pains of muscles and joints associated with simple backache, arthritis strains, bruises and sprains.

WARNINGS

For external use only

DOSAGE AND ADMINISTRATION

Remove the clear backing and apply to thew sore area of skin.

STORAGE AND HANDLING

■ Keep container tightly closed, once opened, fold the opening and keep pressed closed with a clip.
■ Store at room temperature.

Inactive ingredient: Resin

Stop use and ask a doctor if:
■ Condition worsens
■ Symptom clear up and occur again within a few days.
■ Symptom persist for more than 7 days.
■ Nausea, vomiting, abdominal discomfort, diarrhea, or skin rash occurs
■ Excessive irritation of the skin develops
■ When using for pain of arthritis:
■ In conditions affecting children under 12 years of age
■ If red nose is present
■ If pain persists for more than 10 days

KEEP OUT OF REACH OF CHILDREN

Keep out reach of children to avoid accidental poisoning. If swallowed, get medical help or consult a poison control center right away.

Do not use:
■ On wounds
■ On infected or damaged skin
When using this product:
■ Avoid contact with eyes or mucous membranes.
■ Do not bandage tightly.

PURPOSE

EXTERNAL ANALGESIC